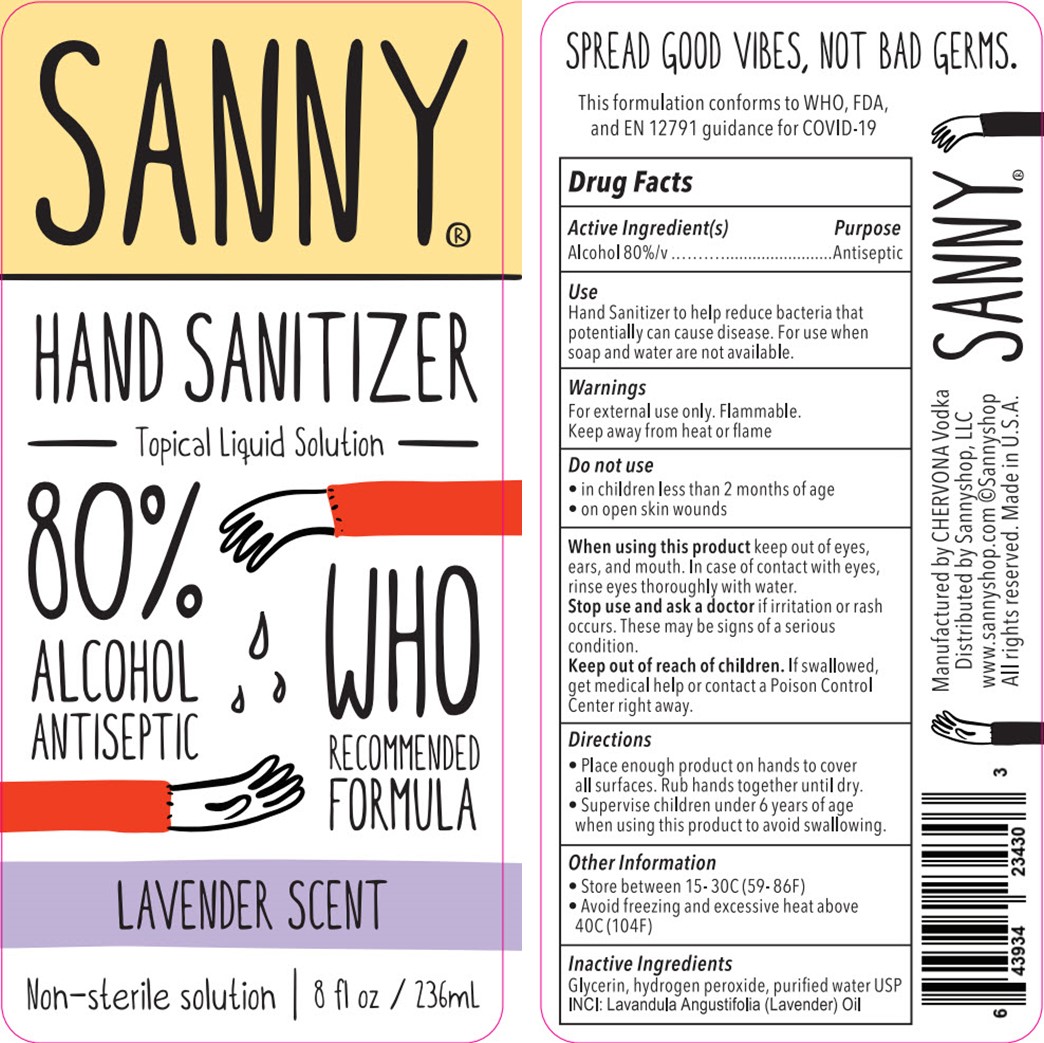 DRUG LABEL: Sanny
NDC: 80367-001 | Form: SOLUTION
Manufacturer: Chervona, LLC
Category: otc | Type: HUMAN OTC DRUG LABEL
Date: 20200917

ACTIVE INGREDIENTS: ALCOHOL 80 mL/100 mL
INACTIVE INGREDIENTS: GLYCERIN 1.45 mL/100 mL; LAVENDER OIL 0.01 mL/100 mL; WATER 18.415 mL/100 mL; HYDROGEN PEROXIDE 0.125 mL/100 mL

Active Indredient(s)

Alcohol 80% v/v

Use

Hand sanitizer to help reduce bacteria that potentially can cause disease. For use when soap and water is not available.

Warnings

For external use only. Flammable. Keep away from heat or flame.

Do not use

- in children less than 2 months of age
- on open skin wounds

When using this product

keep out of eyes, ears, and mouth. In case of contact with eyes, rinse eyes thoroughly with water.

Stop use and ask a doctor

if irritation or rash occurs. These may be signs of a serios condition.

Keep out of reach of children.

If swallowed, get medical help or contact a Poison Control Center right away.

Directions

- Place enough product on hands to cover all surfaces. Rub hands together until dry.
- Supervise children under 6 years of age when using this product to avoid swallowing.

Other Information

- Store between 15-30C (59-86F)
- Avoid freezing and excessive heat above 40C (104F)

Inactive Ingredients

Glycerin, hydrogen peroxide, purified water, lavandula angustifolia (lavender) oil